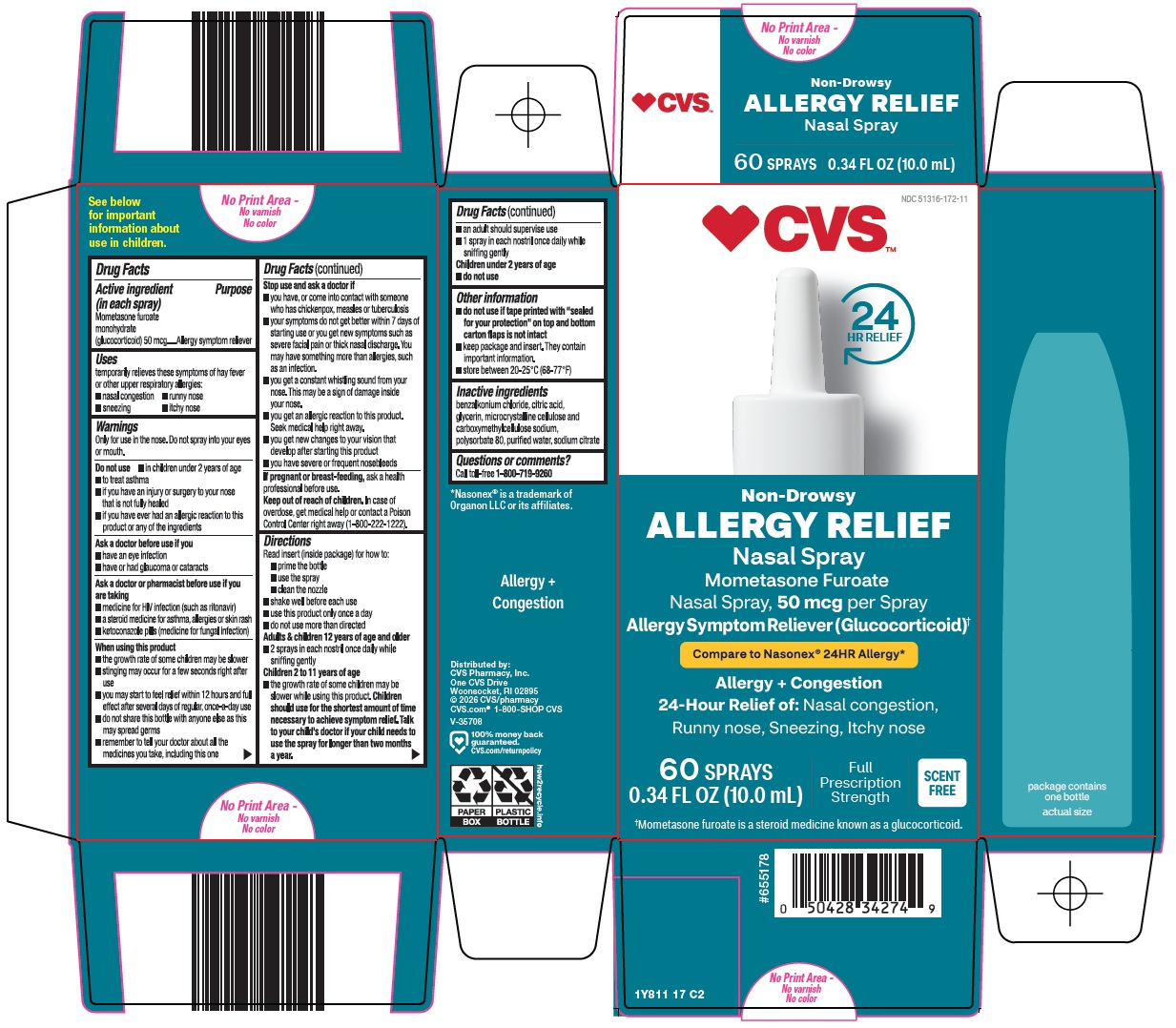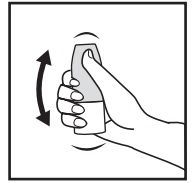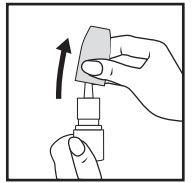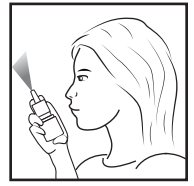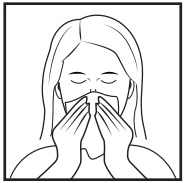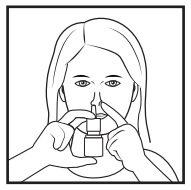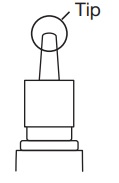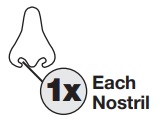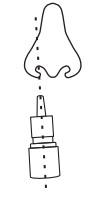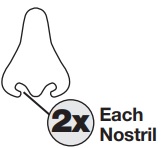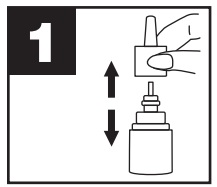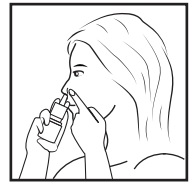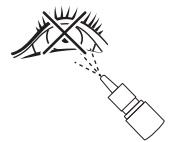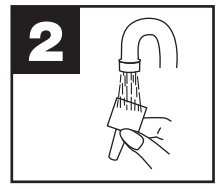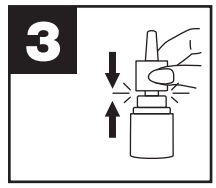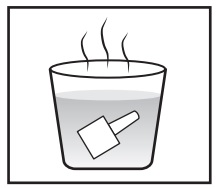 DRUG LABEL: ALLERGY RELIEF
NDC: 51316-172 | Form: SPRAY, METERED
Manufacturer: CVS WOONSOCKET PRESCRIPTION CENTER, INCORPORATED
Category: otc | Type: HUMAN OTC DRUG LABEL
Date: 20260105

ACTIVE INGREDIENTS: MOMETASONE FUROATE MONOHYDRATE 50 ug/1 1
INACTIVE INGREDIENTS: BENZALKONIUM CHLORIDE; CITRIC ACID MONOHYDRATE; GLYCERIN; MICROCRYSTALLINE CELLULOSE; CARBOXYMETHYLCELLULOSE SODIUM, UNSPECIFIED; POLYSORBATE 80; WATER; SODIUM CITRATE, UNSPECIFIED FORM

CVS Pharmacy, Inc. Allergy Relief Drug Facts

Active ingredient (in each spray)

Mometasone furoate monohydrate (glucocorticoid) 50 mcg

Purpose

Allergy symptom reliever

Uses

temporarily relieves these symptoms of hay fever or other upper respiratory allergies:

- nasal congestion
- runny nose
- sneezing
- itchy nose

Warnings

Only for use in the nose. Do not spray into your eyes or mouth.

Do not use

- in children under 2 years of age
- to treat asthma
- if you have an injury or surgery to your nose that is not fully healed
- if you have ever had an allergic reaction to this product or any of the ingredients

Ask a doctor before use if you

- have an eye infection
- have or had glaucoma or cataracts

Ask a doctor or pharmacist before use if you are taking

- medicine for HIV infection (such as ritonavir)
- a steroid medicine for asthma, allergies or skin rash
- ketoconazole pills (medicine for fungal infection)

When using this product

- the growth rate of some children may be slower
- stinging may occur for a few seconds right after use
- you may start to feel relief within 12 hours and full effect after several days of regular, once-a-day use
- do not share this bottle with anyone else as this may spread germs
- remember to tell your doctor about all the medicines you take, including this one

Stop use and ask a doctor if

- you have, or come into contact with someone who has chickenpox, measles or tuberculosis
- your symptoms do not get better within 7 days of starting use or you get new symptoms such as severe facial pain or thick nasal discharge. You may have something more than allergies, such as an infection.
- you get a constant whistling sound from your nose. This may be a sign of damage inside your nose.
- you get an allergic reaction to this product. Seek medical help right away.
- you get new changes to your vision that develop after starting this product
- you have severe or frequent nosebleeds

If pregnant or breast-feeding,

ask a health professional before use.

Keep out of reach of children.

In case of overdose, get medical help or contact a Poison Control Center right away (1-800-222-1222).

Directions

Read insert (inside package) for how to:

- prime the bottle
- use the spray
- clean the nozzle
- shake well before each use
- use this product only once a day
- do not use more than directed
  Adults & children 12 years of age and older
- 2 sprays in each nostril once daily while sniffing gently
  Children 2 to 11 years of age
- the growth rate of some children may be slower while using this product. Children should use for the shortest amount of time necessary to achieve symptom relief. Talk to your child’s doctor if your child needs to use the spray for longer than two months a year.
- an adult should supervise use
- 1 spray in each nostril once daily while sniffing gently
  Children under 2 years of age
- do not use

Other information

- do not use if tape printed with “sealed for your protection” on top and bottom carton flaps is not intact
- keep package and insert. They contain important information.
- store between 20-25° C (68-77° F)

Inactive ingredients

benzalkonium chloride, citric acid, glycerin, microcrystalline cellulose and carboxymethylcellulose sodium, polysorbate 80, purified water, sodium citrate

Questions or comments?

Call toll-free 1-800-719-9260

Consumer information

Mometasone Furoate Nasal Spray, 50 mcg/Spray

1Y800 00 J2

A GETTING STARTED

This product works best at relieving your allergy symptoms when you get a full dose. Here’s how to get started, in five easy steps.

1 SHAKE

Shake spray bottle well.

Remove cap.

2 PRIME

Do this when:

- Starting a new bottle
- Bottle has not been used in one week
- Just cleaned nozzle
Otherwise go to step 3

Aim away from face. Grasp spray bottle as shown. Pump until fine mist appears.

Pumped ten times and still no mist? Spray nozzle may be clogged. See KEEP IT CLEAN, other side.

NOTE: There is enough medicine in the bottle to allow for priming sprays plus the number of sprays

labeled on the bottle.

3 BLOW

Blow nose gently to clear nostrils.

4 AIM

Close one nostril and put tip of spray nozzle in other nostril.

Put just the tip into your nose.

Aim slightly away from center of nose.

5 BREATHE AND SPRAY

While sniffing gently, press down on spray nozzle once or twice (according to dosing instructions).

You’ll feel a light mist in your nose. Breathe out through your mouth.

Repeat in other nostril.

Wipe spray nozzle with clean tissue and replace cap.

Dosing and Cleaning instructions

See other side

SIDE 1

B DIRECTIONS FOR USE

This product works best when you use it daily.

Here’s how to get started.

Children age 2-11

An adult should supervise use

Use one spray in each nostril once daily.

Check with your child’s doctor if child needs to use this product for longer than two months a year.

WARNING:

Do not spray in your eyes. Only for use in your nose.

Users age 12 or older

Use two sprays in each nostril every day.

Other important information for use

- Do not use more than directed.
- If you forget a dose, do not double the next dose.
- Do not spray into eyes or mouth.
- If you get the spray in your eyes, rinse well with water.
- If allergy symptoms do not improve after one week, stop using and talk to a doctor.
- Do not share this bottle with anyone else as this may spread germs.

C KEEP IT CLEAN

A clean spray nozzle helps ensure a full dose. Clean it weekly, or if it's clogged. Don't try to unblock nozzle with pin or sharp object – that can damage it.

Remove spray nozzle by grasping at base and pulling up.

Rinse under running tap water, and dry at room temperature.

Aim away from your face and gently, but firmly replace spray nozzle.

If spray nozzle is clogged, soak in warm water. Then repeat steps 2 and 3.

Questions or comments? Call toll-free 1-800-719-9260

Store between 20º-25ºC (68º-77ºF)

Distributed By

Perrigo®

Allegan, MI 49010

SIDE 2

Package/Label Principal Display Panel

CVS™

24 HR RELIEF

Non-Drowsy

ALLERGY RELIEF

Nasal Spray

Mometasone Furoate

Nasal Spray, 50 mcg per Spray

Allergy Symptom Reliever (Glucocorticoid)†

Compare to Nasonex® 24HR Allergy

Allergy + Congestion

24-Hour Relief of: Nasal congestion, Runny nose, Sneezing, Itchy nose

60 SPRAYS

0.34 FL OZ (10.0 mL)

Full Prescription Strength

SCENT FREE

†Mometasone furoate is a steroid medicine known as a glucocorticoid.